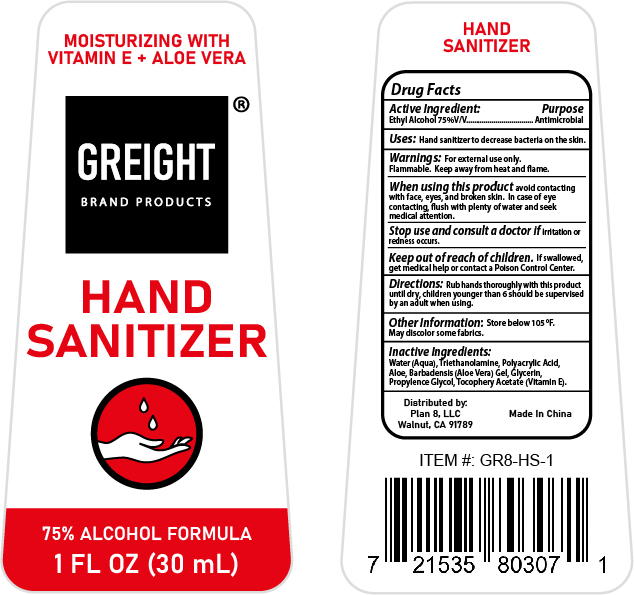 DRUG LABEL: Hand Sanitizer
NDC: 77972-101 | Form: LIQUID
Manufacturer: Zhejiang Taoyel Biological Technology Co., Ltd.
Category: otc | Type: HUMAN OTC DRUG LABEL
Date: 20200601

ACTIVE INGREDIENTS: ALCOHOL 75 mL/100 mL
INACTIVE INGREDIENTS: POLYACRYLIC ACID (250000 MW); ALOE VERA LEAF; GLYCERIN; WATER; AMINOMETHYLPROPANOL; PROPYLENE GLYCOL; .ALPHA.-TOCOPHEROL ACETATE

hand sanitizer

hand sanitizer

Active Ingredient:

Alcohol 75% v/v

Purpose

Antimicrobial

Uses:

Hand sanitizer to decrease bacteria on the skin.

Warnings:

For external use only. Flammable. Keep away from heat or flame

When using this product

avoid contacting with face, eyes, and broken skin. In case of eye contacting, flush with plenty of water and seek medical attention.

Stop use and consut a doctor if

irritation or redness occurs.

Keep out of reach of children.

If swallowed, get medical help or contact a Poison Control Center.

Directions:

Rub hands thoroughlywith this product until dry, children younger than 6 should be supervised by an adult when using.

Other information:

Store below 105ºF. May discolor some fabrics.

Inactive ingredients:

Water (Aqua), Triethanolamine, Polyacrylic Adcid, Aloe Barbadensis (Aloe Vera) Gel, Glycerin, Propylence Glycol, Tocophery Acetate (Vitamin E).